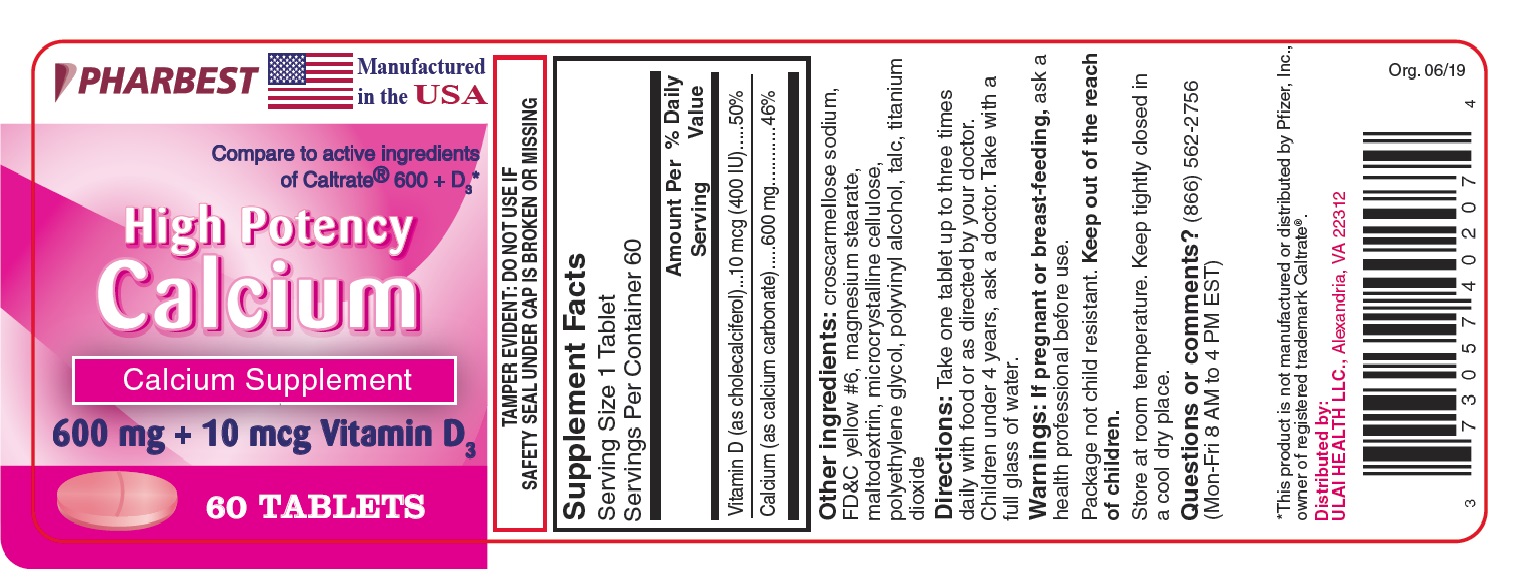 DRUG LABEL: High Potency Calcium
NDC: 73057-402 | Form: TABLET, FILM COATED
Manufacturer: Ulai Health LLC
Category: other | Type: DIETARY SUPPLEMENT
Date: 20190723

ACTIVE INGREDIENTS: CHOLECALCIFEROL 10 ug/1 1; CALCIUM CARBONATE 600 mg/1 1
INACTIVE INGREDIENTS: CROSCARMELLOSE SODIUM; FD&C YELLOW NO. 6; MAGNESIUM STEARATE; MALTODEXTRIN; CELLULOSE, MICROCRYSTALLINE; POLYETHYLENE GLYCOL, UNSPECIFIED; POLYVINYL ALCOHOL, UNSPECIFIED; TALC; TITANIUM DIOXIDE

Supplement Facts

Serving Size 1 Tablet

Servings Per Container 60

 | Amount Per Serving | % Daily Value
Vitamin D (as cholecalciferol) | 10 mcg (400 IU) | 50%
Calcium (as calcium carbonate) | 600 mg | 46%

Other ingredients: croscarmellose sodium, FD&C yellow #6, magnesium stearate, maltodextrin, microcrystalline cellulose, polyethylene glycol, polyvinyl alcohol, talc, titanium dioxide

DOSAGE AND ADMINISTRATION

Take one tablet up to three times daily with food or as directed by your doctor. Children under 4 years, ask a doctor.

Take with a full glass of water.

WARNINGS

If pregnant or breast-feeding, ask a health professional before use.

Package not child resistant.

Keep out of the reach of children.

SAFE HANDLING WARNING

Store at room temperature. Keep tightly closed in a cool dry place.

Questions or comments? (866) 562-2756 (Mon-Fri 8 AM to 4 PM EST)

PACKAGE LABEL

PHARBEST

Manufactured in the USA

Compare to active ingredients of Caltrate® 600 + D3*

High Potency

Calcium

Calcium Supplement

600 mg + 10 mcg Vitamin D3

60 TABLETS